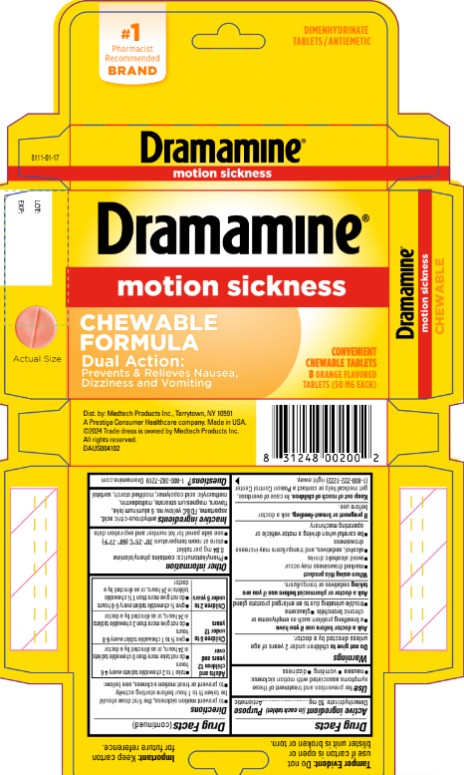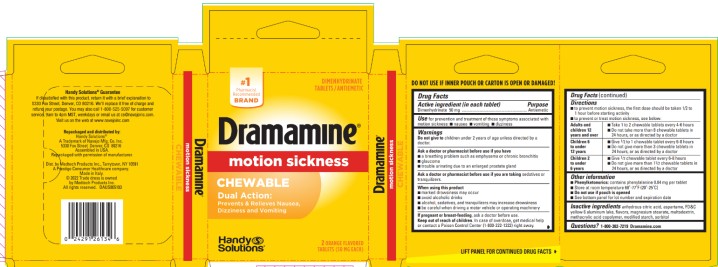 DRUG LABEL: Dramamine Orange
NDC: 63029-902 | Form: TABLET, CHEWABLE
Manufacturer: Medtech Products Inc.
Category: otc | Type: HUMAN OTC DRUG LABEL
Date: 20250910

ACTIVE INGREDIENTS: DIMENHYDRINATE 50 mg/1 1
INACTIVE INGREDIENTS: ANHYDROUS CITRIC ACID; ASPARTAME; FD&C YELLOW NO. 6; ALUMINUM OXIDE; MAGNESIUM STEARATE; MALTODEXTRIN; SORBITOL

Dramamine Chewable Orange

Drug Facts

Active ingredient

(in each tablet)

Dimenhydrinate 50 mg

Purpose

Antiemetic

Use

for prevention and treatment of these symptoms associated with motion sickness

- nausea
- vomiting
- dizziness

Warnings

Do not give to

children under 2 years of age unless directed by a doctor

Ask a doctor before use if you have

- a breathing problem such as emphysema or chronic bronchitis
- glaucoma
- trouble urinating due to an enlarged prostate gland

Ask a doctor or pharmacist before use

if you are taking sedatives or tranquilizers

When using this product

- marked drowsiness may occur
- avoid alcoholic drinks
- alcohol, sedatives, and tranquilizers may increase drowsiness
- be careful when driving a motor vehicle or operating machinery

If pregnant or breast-feeding,

ask a doctor before use.

Keep out of reach of children.

In case of accidental overdose, get medical help or contact a Poison Control Center (1-800-222-1222) right away.

Directions

to prevent motion sickness, the first dose should be taken ½ to 1 hour before starting activity

to prevent or treat motion sickness, see below:

Adults and children 12 years and over | - take 1 to 2 tablets every 4-6 hours - do not take more than 8 chewable tablets in 24 hours, or as directed by a doctor
Children 6 to under 12 years | - give ½ to 1 tablet every 6-8 hours - do not give more than 3 chewable tablets in 24 hours, or as directed by a doctor
Children 2 to under 6 years | - give ½ tablet every 6-8 hours - do not give more than 1 ½ chewable tablets in 24 hours, or as directed by a doctor

Other information

- Phenylketonurics: contains phenylalanine 0.84 mg per tablet
- store at room temperature 68-77ºF (20-25ºC)
- do not use if carton is opened or if blister is broken or torn
- see side panel for lot number and expiration date

Inactive ingredients

anhydrous citric acid, aspartame, FD&C yellow #6 aluminum lake, flavors, magnesium stearate, maltodextrin, methacrylic acid copolymer, modified starch, sorbitol

Questions or comments?

Call 1-800-382-7219

PRINCIPAL DISPLAY PANEL

Dimenhydrinate Tablets/Antiemetic
CHEWABLE FORMULA
Dramamine®
MOTION SICKNESS RELIEF
DUAL ACTION
1. TREATS SYMPTOMS ON THE SPOT
2. PREVENTS NAUSEA, DIZZINESS & VOMITING
Convenient Chewable Tablets
8 ORANGE FLAVORED TABLETS (50 mg EACH)

PRINCIPAL DISPLAY PANEL

Dimenhydrinate Tablets/Antiemetic
CHEWABLE FORMULA
Dramamine®
MOTION SICKNESS RELIEF
DUAL ACTION
1. TREATS SYMPTOMS ON THE SPOT
2. PREVENTS NAUSEA, DIZZINESS & VOMITING
Convenient Chewable Tablets
2 ORANGE FLAVORED TABLETS (50 mg EACH)